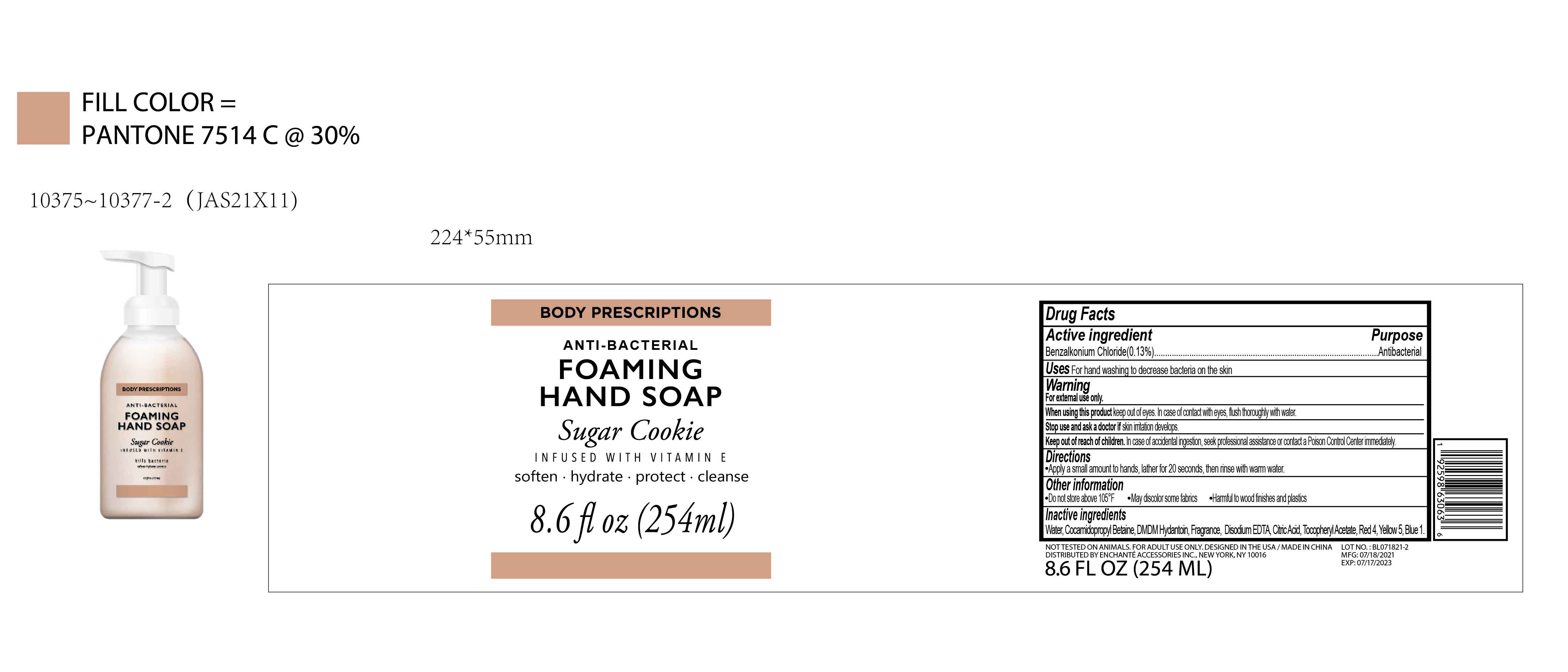 DRUG LABEL: BODY PRESCRIPTIONS Sugar Cookie INFUSED WITH VITAMIN E ANTIBACTERIAL FOAMING HAND
NDC: 50563-458 | Form: SOAP
Manufacturer: ENCHANTE ACCESSORIES INC.
Category: otc | Type: HUMAN OTC DRUG LABEL
Date: 20210704

ACTIVE INGREDIENTS: BENZALKONIUM CHLORIDE 0.13 g/100 mL
INACTIVE INGREDIENTS: COCAMIDOPROPYL BETAINE; DMDM HYDANTOIN; DISODIUM HEDTA; CITRIC ACID MONOHYDRATE; .ALPHA.-TOCOPHEROL ACETATE; WATER; FD&C YELLOW NO. 5; FD&C RED NO. 4; FD&C BLUE NO. 1

50563-458/JAS21X11

Active Ingredient

Benzalkonium Chloride 0.13%

Purpose

Antibacterial

Use

■ For hand washing to decrease bacteria on the skin

WARNINGS

For external use only

When using this product, keep out of eyes. In case of contact with eyes, flush thoroughly with water.

Stop use and ask a doctor if skin irritation develops.

Keep out of reach of children. In case of accidenta ingestion, seek professional assistance or contact a Poison Control Center immdiately.

Directions

Apply a small amount to hands, lather for 20 seconds, then rinse with warm water.

Other Information

Do not store above 105F

May discolor some fabrics

Harmful to wood finishes and plastics

Inactive ingredients

Water, Cocamidopropyl Betaine, DMDM Hydantoin, Fragrance, Disodium EDTA, Citric Acid, Tocopheryl Acetate, Red 4, Yellow 5, Blue 1